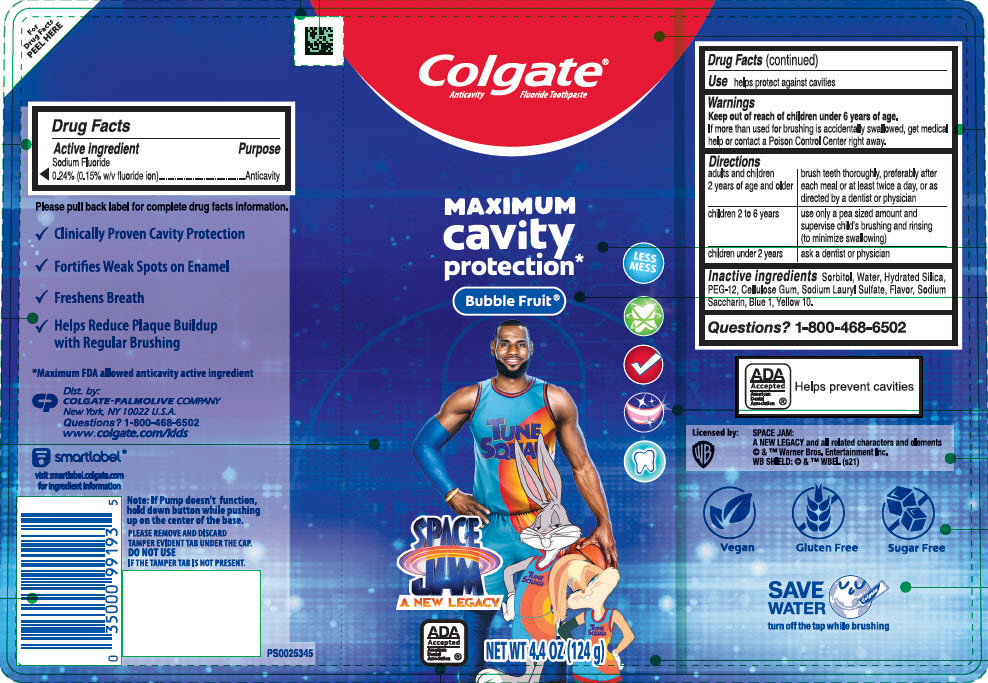 DRUG LABEL: Colgate Kids Space Jam
NDC: 35000-199 | Form: GEL, DENTIFRICE
Manufacturer: Colgate-Palmolive Company
Category: otc | Type: HUMAN OTC DRUG LABEL
Date: 20241114

ACTIVE INGREDIENTS: SODIUM FLUORIDE 1.1 mg/1 g
INACTIVE INGREDIENTS: SORBITOL 476 mg/1 g; WATER; HYDRATED SILICA; POLYETHYLENE GLYCOL 600; CARBOXYMETHYLCELLULOSE; SODIUM LAURYL SULFATE; SACCHARIN SODIUM; FD&C BLUE NO. 1; D&C YELLOW NO. 10

Colgate® Kids Space Jam
Mild Bubble Fruit® Flavor

Drug Facts

Active ingredient

Sodium Fluoride 0.24% (0.15% w/v fluoride ion)

Purpose

Anticavity

Use

helps protect against cavities

Warnings

Keep out of reach of children under 6 years of age.

If more than used for brushing is accidentally swallowed, get medical help or contact a Poison Control Center right away.

Directions

adults and children 2 years of age and older | brush teeth thoroughly, preferably after each meal or at least twice a day, or as directed by a dentist or physician
children 2 to 6 years | use only a pea sized amount and supervise child's brushing and rinsing (to minimize swallowing)
children under 2 years | ask a dentist or physician

Inactive ingredients

Sorbitol, Water, Hydrated Silica, PEG-12, Cellulose Gum, Sodium Lauryl Sulfate, Flavor, Sodium Saccharin, Blue 1, Yellow 10.

Questions?

1-800-468-6502

Dist. by:
COLGATE-PALMOLIVE COMPANY
New York, NY 10022

PRINCIPAL DISPLAY PANEL - 124 g Tube Label

Colgate®
Anticavity Fluoride Toothpaste

MAXIMUM
cavity
protection*

Bubble Fruit®

LESS
MESS

SPACE
JAM
A NEW LEGACY

ADA
Accepted
American
Dental
Association ®

NET WT 4.4 OZ (124 g)